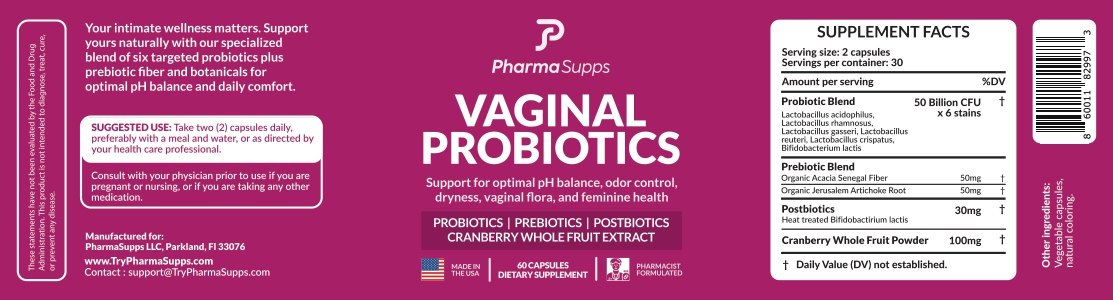 DRUG LABEL: Vaginal Probiotics
NDC: 87260-003 | Form: CAPSULE
Manufacturer: PharmaSupps LLP
Category: other | Type: Dietary Supplement
Date: 20260116

ACTIVE INGREDIENTS: ACACIA 50 mg/1 1; CRANBERRY 100 mg/1 1

Vaginal Probiotics

STATEMENT OF IDENTITY

This statement have not been evaluated by the Food and Drug Administration. This product is not intended to diagnose, treat, cure or prevent any disease.